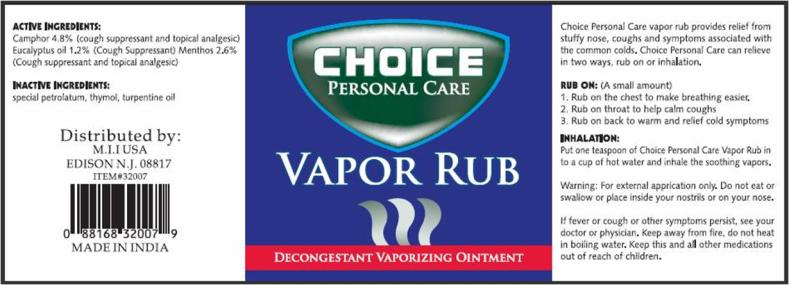 DRUG LABEL: Choice Personal Care Vapor Rub
NDC: 51628-3232 | Form: GEL
Manufacturer: My Import Inc
Category: otc | Type: HUMAN OTC DRUG LABEL
Date: 20101105

ACTIVE INGREDIENTS: CAMPHOR (NATURAL) 5.4 g/1 g; EUCALYPTUS OIL 1.4 g/1 g; MENTHOL 3 g/1 g
INACTIVE INGREDIENTS: THYMOL; TURPENTINE; PETROLATUM

Vapor Rub

Choice Personal Care vapor rub provides relief from stuffy nose, coughs and symptoms associated with the common colds. Choice Personal Care can relieve in two ways, rub on or inhalation.

RUB ON:

(A small amount)

1. Rub on the chest to make breathing easier.
2. Rub on the throat to help calm coughs
3. Rub on back to warm and relief cold symptoms

INHALATION

Put one teaspoon of Choice Personal Care Vapor Rub in to a cup of hot water and inhale the soothing vapors.

Warning:

For external application only.

Do not

eat or swallow or place inside your nostrils on your nose.

If fever or cough or other symptoms persist, see your doctor or physician.

Keep away from fire, do not heat in boiling water.

Active Ingredients:

Camphor 4.8%

Purpose:

(cough suppressant and topical analgesic)

Active Ingredients:

Eucalyptus oil 1.2%

Purpose:

(Cough Suppressant)

Active Ingredients:

Menthos 2.6%

Purpose:

(cough suppressant and topical analgesic)

Inactive Ingredients:

special petrolatum, thymol, turpentine oil

PRINCIPAL DISPLAY PANEL

CHOICE PERSONAL CARE
VAPOR RUB
DECONGESTANT VAPORIZING OINTMENT